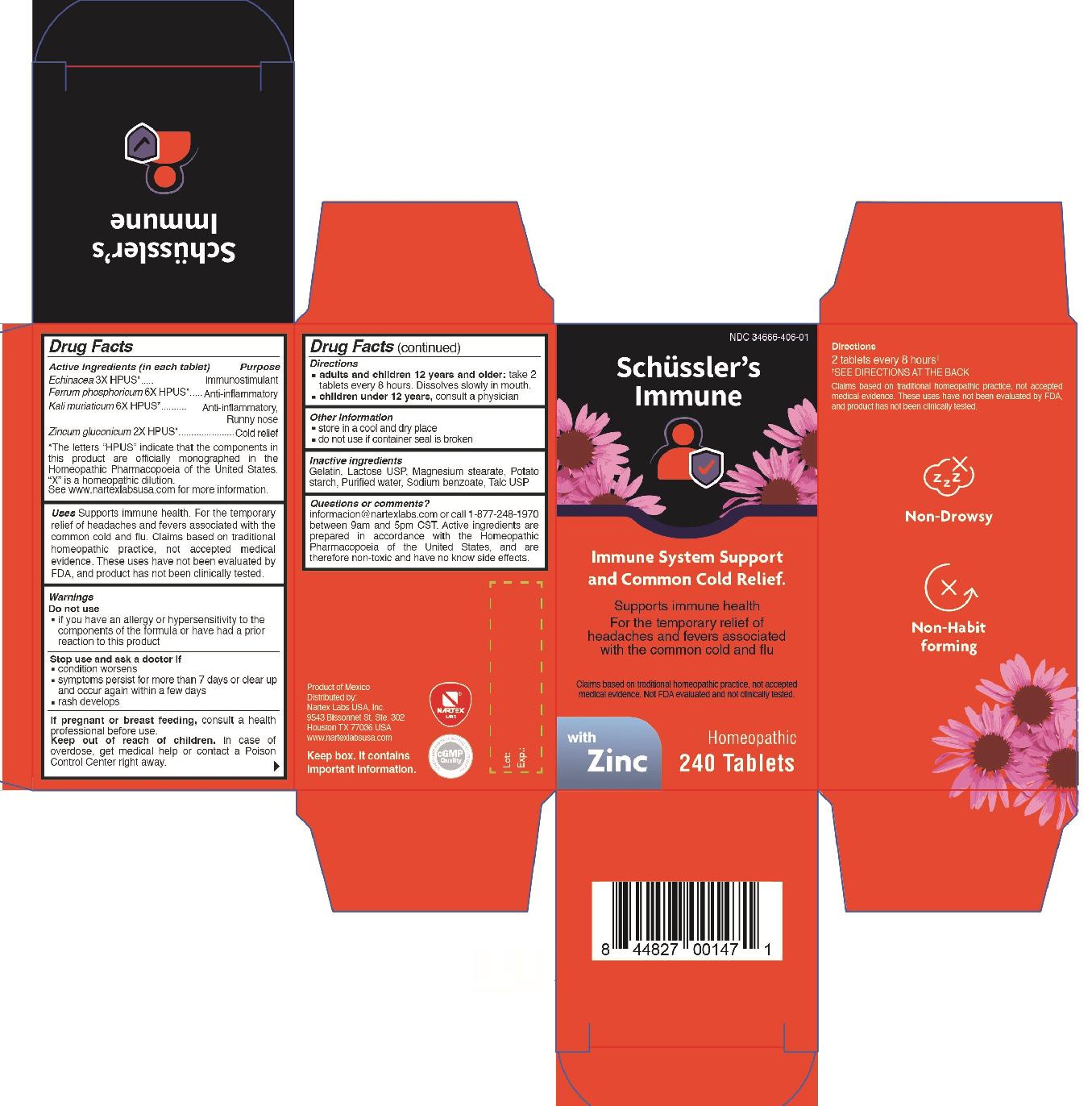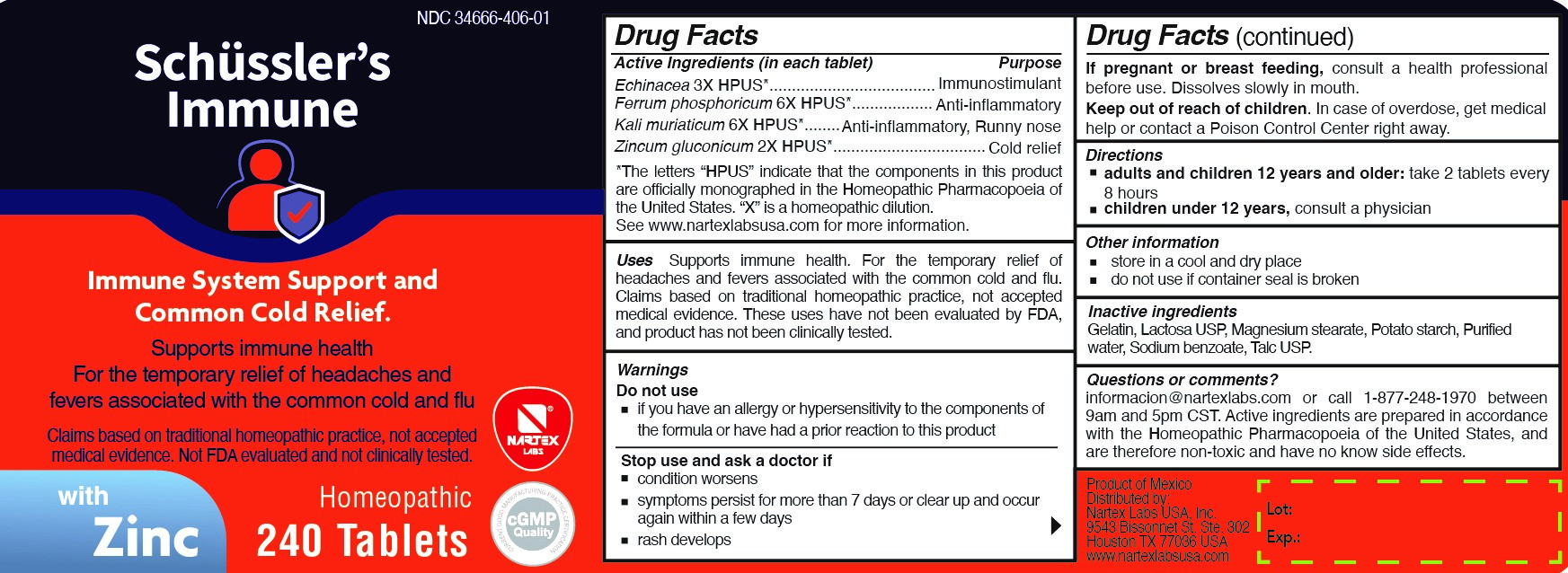 DRUG LABEL: Schusslers Immune
NDC: 34666-406 | Form: TABLET
Manufacturer: Nartex Laboratorios Homeopaticos, S.A. de C.V.
Category: homeopathic | Type: HUMAN OTC DRUG LABEL
Date: 20220113

ACTIVE INGREDIENTS: FERROSOFERRIC PHOSPHATE 6 [hp_X]/1 1; POTASSIUM CHLORIDE 6 [hp_X]/1 1; ZINC GLUCONATE 2 [hp_X]/1 1; ECHINACEA, UNSPECIFIED 3 [hp_X]/1 1
INACTIVE INGREDIENTS: LACTOSE, UNSPECIFIED FORM; MAGNESIUM STEARATE; STARCH, POTATO; WATER; SODIUM BENZOATE; TALC; GELATIN

Schussler's Immune

Active ingredients

Echinacea 3X HPUS*

Ferrum phosphoricum 6X HPUS*

Kali muriaticum 6X HPUS*

Zincum gluconicum 2X HPUS*

* The letters "HPUS" indicate that the components in this product are officially monographed in the Homeopathic Pharmacopoeia of the United States. "X" is a homeopathic dilution. See www.nartexlabsusa.com for more information.

Purpose

Echinacea 3X HPUS*................................Immunostimulant

Ferrum phosphoricum 6X HPUS*....................................Anti-inflammatory

Kali muriaticum 6X HPUS*........................Anti-inflammatory, Runny nose

Zincum gluconicum 2X HPUS*..............................Cold relief

* The letters "HPUS" indicate that the components in this product are officially monographed in the Homeopathic Pharmacopoeia of the United States. "X" is a homeopathic dilution. See www.nartexlabsusa.com for more information.

Uses

Supports immune health For the temporary relief of headaches and fevers associated with the common cold and flu. Claims based on traditional homeopathic practice, not accepted medical evidence. These uses have not been evaluated by FDA, and product has not been clinically tested.

Warnings

Do not use

- if you have an allergy or hypersensitivity to the components of the formula or have had a prior reaction to this product

Stop use and ask a doctor if

- condition worsens
- symptoms persist for more than 7 days or clear up and occur again within a few days
- rash develops

PREGNANCY OR BREAST FEEDING

If pregnant or breast feeding, consult a health professional before use.

Keep out of reach of children. In case of overdose, get medical help or contact a Poison Control Center right away.

Directions

- adults and children 12 years and older: take tablets every 8 hours. Dissolves slowly in mouth.
- childrenunder 12 years, consult a physician

Other information

- store in a cool and dry place
- do not use if container seal is broken

Inactive ingredients

Gelatin, Lactose USP, Magnesium stearate, Potato starch, Purified water, Sodium benzoate, Talc USP

Questions or comments?

informacion@nartexlabs.com or call 1-877-248-1970 between 9am and 5pm CST. Active ingredients are prepared in accordance with the Homeopathic Pharmacopoeia of the United States, and are therefore non-toxic and have no known side effects.

PACKAGE LABEL

NDC 34666-406-01

Schussler's Immune

Immune System Support and Common Cold Relief.

Supports immune health

For the temporary relief of headaches and fevers associated with the common cold and flu

Claims based on traditional homeopathic practice, not accepted medical evidence. Not FDA evaluated and not clinically tested.

with Zinc

Homeopathic

240 Tablets